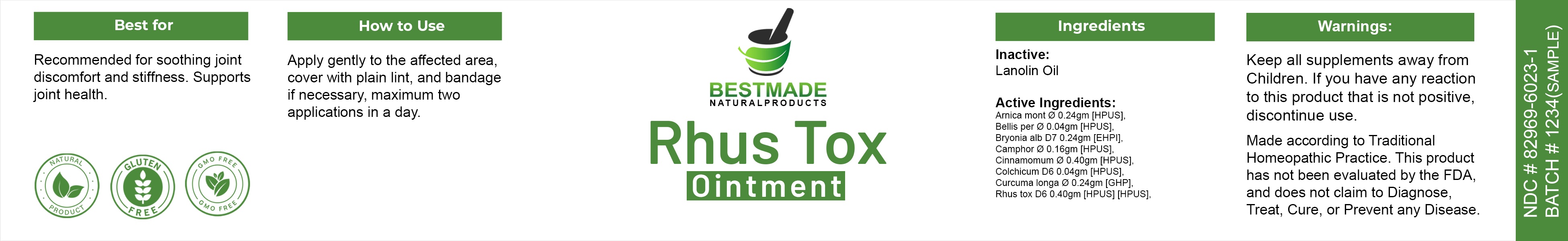 DRUG LABEL: Bestmade Natural Products Rhus Tox
NDC: 82969-6023 | Form: OINTMENT
Manufacturer: Bestmade Natural Products
Category: homeopathic | Type: HUMAN OTC DRUG LABEL
Date: 20241219

ACTIVE INGREDIENTS: BELLIS PERENNIS LEAF 0.04 g/40 g; CINNAMON 0.4 g/40 g; ARNICA MONTANA FLOWER 0.24 g/40 g; BRYONIA ALBA WHOLE 0.24 g/40 g; CAMPHOR (NATURAL) 0.16 g/40 g; TOXICODENDRON PUBESCENS LEAF 0.04 g/40 g; COLCHICUM AUTUMNALE FLOWER 0.04 g/40 g; CURCUMA LONGA LEAF 0.24 g/40 g
INACTIVE INGREDIENTS: LANOLIN 40 g/40 g

Rhus Tox Ointment

DOSAGE AND ADMINISTRATION

Apply gently to the arrected area cover with plain lint, and bandage If necessary, maximum two applications in a day.

INDICATIONS AND USAGE

Best for
Recommended for soothing joint discomfort and stiffness. Supports joint health.

Inactive ingredients

Lanolin Oil

Active Ingredients:
Amica mont ø 0.24gm [HPUS]
Bellis per ø 0.04gm [HPUS).
Bryonia alb D7 0.24gm [EHPI].
Camphor ø 0.16gm [HPUS].
Cinnamomum ø 0.40gm [HPUS].
Colchicum D6 0.04gm [HPUS),

Curcuma longa ø 0.24gm [GHP]
Rhus tox D6 0.40gm [HPUS] [HPUS).

Warnings

Keep all supplements away from Children.

If you have any reaction to this product that is not positive, discontinue use.

Made according to Traditional Homeopathic Practice. This product has not been evaluated by the FDA and does not claim to Diagnose, Treat, Cure, or Prevent any Disease.

PURPOSE

Best for

Recommended for soothing joint discomfort and stiffness. Supports joint health.

Warnings

Keep all supplements away from Children.

If you have any reaction to this product that is not positive, discontinue use.

Made according to Traditional Homeopathic Practice. This product has not been evaluated by the FDA and does not claim to Diagnose, Treat, Cure, or Prevent any Disease.

Entire package label